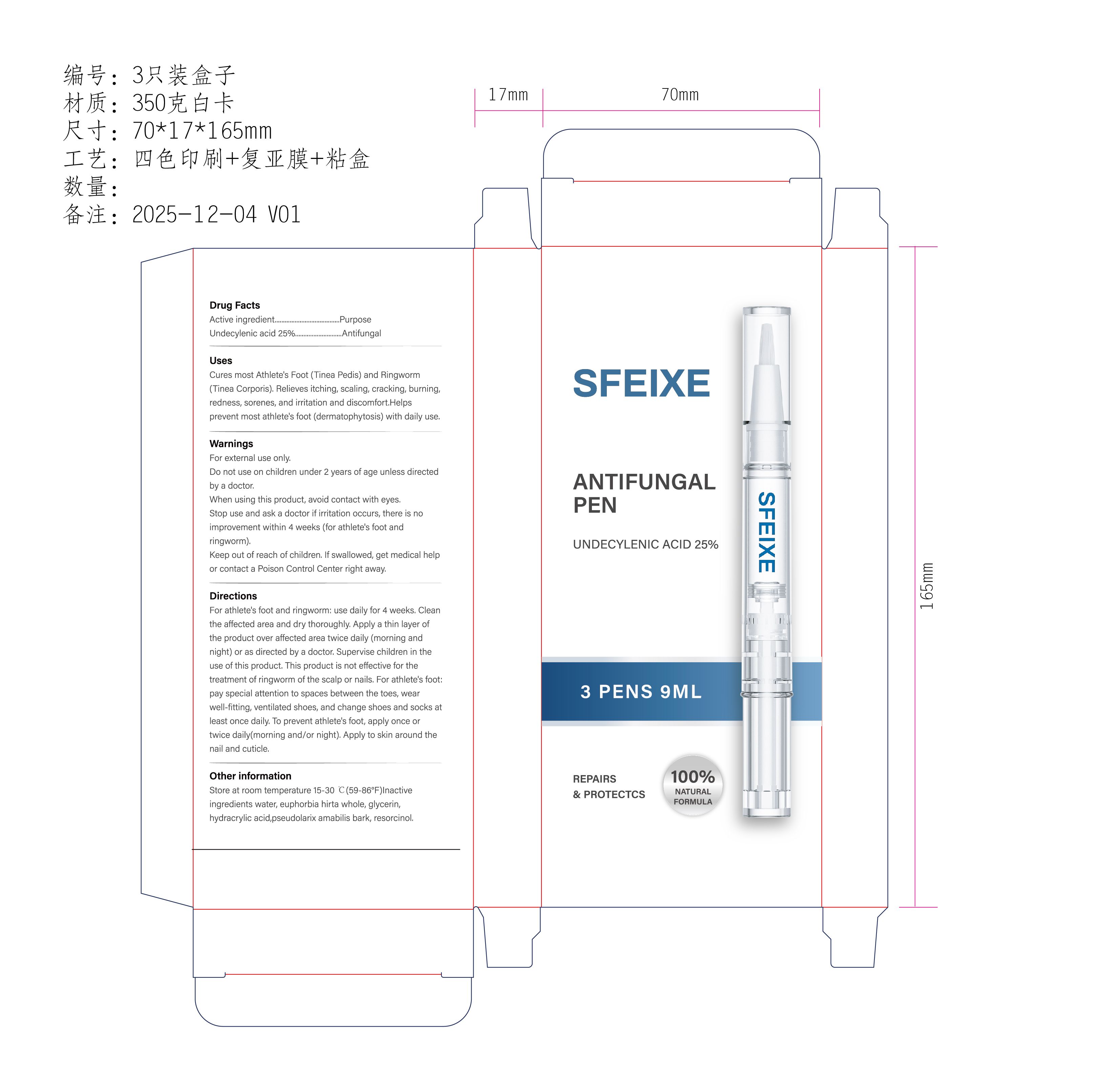 DRUG LABEL: SFEIXE ANTIFUNGAL PEN
NDC: 87259-001 | Form: PASTE
Manufacturer: Zhejiang JOOZENA Medical Technology Co., Ltd.		
Category: otc | Type: HUMAN OTC DRUG LABEL
Date: 20260212

ACTIVE INGREDIENTS: UNDECYLENIC ACID 25 g/100 mL
INACTIVE INGREDIENTS: RESORCINOL; WATER; HYDRACRYLIC ACID; EUPHORBIA HIRTA WHOLE; PSEUDOLARIX AMABILIS BARK; GLYCERIN

ACTIVE INGREDIENT

UNDECYLENIC ACID 25%

PURPOSE

Cures most Athlete's Foot (Tinea Pedis) and Ringworm(Tinea Corporis). Relieves itching, scaling, cracking, burning,redness, sorenes, and irritation and discomfort.Helpsprevent most athlete's foot (dermatophytosis) with daily use.

Keep out of reach of children. lf swallowed, get medical helpor contact a Poison Control Center right away.

Warnings
For external use only.
Do not use on children under 2 years of age unless directedby a doctor.
When using this product, avoid contact with eyes.Stop use and ask a doctor if irritation occurs, there is noimprovement within 4 weeks (for athlete's foot andringworm).

INDICATIONS AND USAGE

This product is not effective for thetreatment of ringworm of the scalp or nails. For athlete's foot:pay special attention to spaces between the toes, wearwell-fitting, ventilated shoes, and change shoes and socks atleast once daily. To prevent athlete's foot, apply once ortwice daily(morning and/or night). Apply to skin around thenail and cuticle.

DOSAGE AND ADMINISTRATION

For athlete's foot and ringworm: use daily for 4 weeks, Cleanthe affected area and dry thoroughly. Apply a thin layer ofthe product over affected area twice daily (morning andnight) or as directed by a doctor. Supervise children in theuse of this product,

INACTIVE INGREDIENT

water, euphorbia hirta whole, glycerin,hydracrylic acid,pseudolarix amabilis bark, resorcinol,